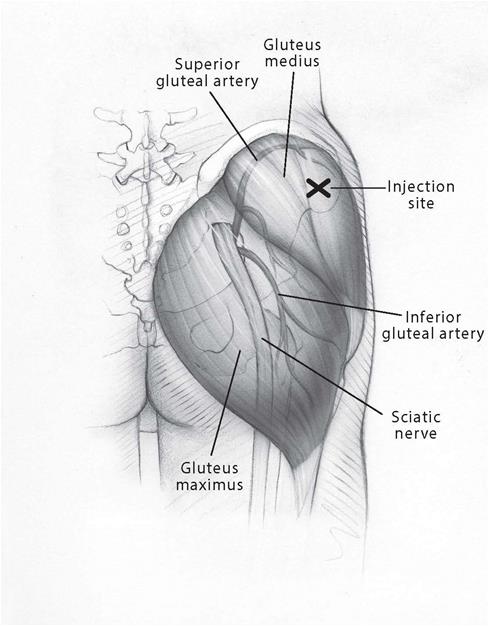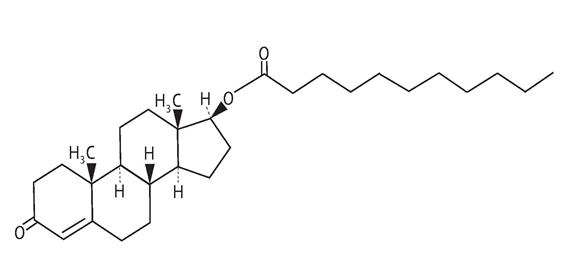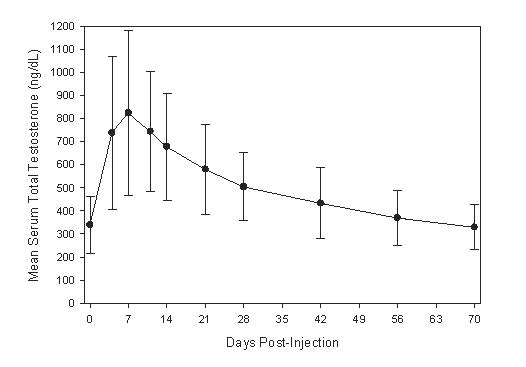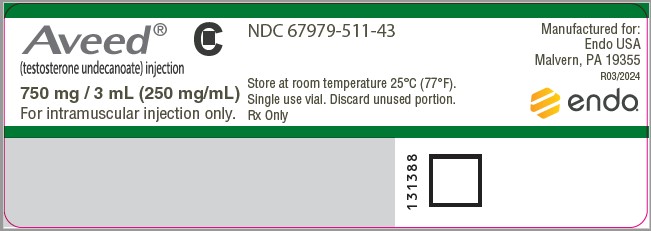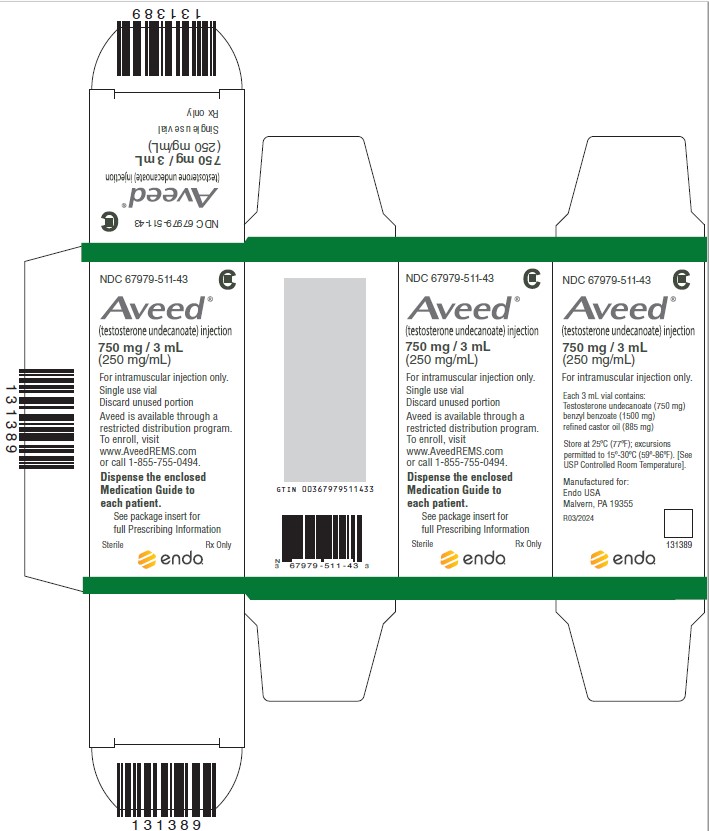 DRUG LABEL: Aveed
NDC: 67979-511 | Form: INJECTION
Manufacturer: Endo USA, Inc.
Category: prescription | Type: HUMAN PRESCRIPTION DRUG LABEL
Date: 20250715
DEA Schedule: CIII

ACTIVE INGREDIENTS: TESTOSTERONE UNDECANOATE 250 mg/1 mL
INACTIVE INGREDIENTS: CASTOR OIL; BENZYL BENZOATE

HIGHLIGHTS OF PRESCRIBING INFORMATION

These highlights do not include all the information needed to use AVEED® safely and effectively. See full prescribing information for AVEED®.
AVEED® (testosterone undecanoate) injection, for intramuscular use
CIII
Initial U.S. Approval: 1953

WARNING: SERIOUS PULMONARY OIL MICROEMBOLISM (POME) REACTIONS AND ANAPHYLAXIS

See full prescribing information for complete boxed warning

- Serious POME reactions, involving urge to cough, dyspnea, throat tightening, chest pain, dizziness, and syncope; and episodes of anaphylaxis, including life-threatening reactions, have been reported to occur during or immediately after the administration of testosterone undecanoate injection. These reactions can occur after any injection of testosterone undecanoate during the course of therapy, including after the first dose (5.1).
- Following each injection of Aveed, observe patients in the healthcare setting for 30 minutes in order to provide appropriate medical treatment in the event of serious POME reactions or anaphylaxis (5.1).
- Aveed is available only through a restricted program called the Aveed REMS Program (5.2).

1 INDICATIONS AND USAGE

Aveed (testosterone undecanoate) injection is an androgen indicated for testosterone replacement therapy in adult males for conditions associated with a deficiency or absence of endogenous testosterone:

- Primary hypogonadism (congenital or acquired) (1)
- Hypogonadotropic hypogonadism (congenital or acquired) (1)

Aveed should only be used in patients who require testosterone replacement therapy and in whom the benefits of the product outweigh the serious risks of pulmonary oil microembolism and anaphylaxis (1).

Limitations of Use

- Safety and efficacy of Aveed in men with “age-related hypogonadism” have not been established (1).
- Safety and efficacy of Aveed in males less than 18 years old have not been established (1, 8.4).

RECENT MAJOR CHANGES

Warnings and Precautions, Venous Thromboembolism (5.4) 07/2025

Warnings and Precautions, Blood Pressure Increases (5.6) 07/2025

Warnings and Precautions, Cardiovascular Risk (5.6) Removed 07/2025

2 DOSAGE AND ADMINISTRATION

- Prior to initiating Aveed, confirm the diagnosis of hypogonadism by ensuring that serum testosterone has been measured in the morning on at least two separate days and that these concentrations are below the normal range (2).
- For intramuscular use only (2.1).
- Three (3) mL (750 mg) is to be injected intramuscularly at initiation, at 4 weeks, and every 10 weeks thereafter (2.1).
- Following each injection of Aveed, observe patients in the healthcare setting for 30 minutes in order to provide appropriate medical treatment in the event of serious POME reactions or anaphylaxis (2.3).
- Inject Aveed deeply into the gluteal muscle following the usual precautions for intramuscular administration of oily solutions (2.3).

3 DOSAGE FORMS AND STRENGTHS

- 750 mg/3 mL (250 mg/mL) testosterone undecanoate sterile injectable solution is provided in an amber glass, single use vial with silver-colored crimp seal and gray plastic cap (3).

4 CONTRAINDICATIONS

- Men with carcinoma of the breast or known or suspected carcinoma of the prostate (4, 5.5).
- Women who are pregnant. Testosterone may cause fetal harm (4, 5.8, 8.1, 8.2).
- Known hypersensitivity to Aveed or its ingredients (testosterone undecanoate, refined castor oil, benzyl benzoate) (4).

5 WARNINGS AND PRECAUTIONS

- Venous thromboembolism (VTE): VTE, including deep vein thrombosis (DVT) and pulmonary embolism (PE), have been reported in patients using testosterone products. Evaluate patients with signs or symptoms consistent with DVT or PE (5.4).
- Worsening of Benign Prostatic Hyperplasia (BPH) and Potential Risk of Prostate Cancer: Monitor patients with BPH for worsening of signs and symptoms of BPH (5.5).
- Blood Pressure Increases: Testosterone can increase blood pressure, which can increase cardiovascular risk over time. Measure blood pressure periodically. Not recommended for use in men with uncontrolled hypertension (5.6)
- Abuse of Testosterone: Testosterone has been subject to abuse, typically at doses higher than recommended for the approved indication and in combination with other anabolic androgenic steroids (5.7).
  Potential for Adverse Effects on Spermatogenesis:
- Exogenous administration of androgens may lead to azoospermia (5.9).
- Edema: Edema with or without congestive heart failure may be a complication in patients with preexisting cardiac, renal, or hepatic disease (5.11).
- Sleep apnea: Sleep apnea may occur in those with risk factors (5.13).
- Monitor prostatic specific antigen (PSA), hemoglobin, hematocrit, and lipid concentrations periodically (5.3, 5.5, 5.14).

6 ADVERSE REACTIONS

The most commonly reported adverse reactions (≥2%) are acne, injection site pain, prostatic specific antigen (PSA) increased, estradiol increased, hypogonadism, fatigue, irritability, hemoglobin increased, insomnia, and mood swings (6.1).

To report SUSPECTED ADVERSE REACTIONS, contact Endo at 1-800-462-3636 or FDA at 1-800-FDA-1088 or www.fda.gov/medwatch.

7 DRUG INTERACTIONS

- Androgens may decrease blood glucose, and therefore may decrease insulin requirements in diabetic patients (7.1).
- Changes in anticoagulant activity may be seen with androgens. More frequent monitoring of international normalized ratio (INR) and prothrombin time is recommended in patients taking warfarin (7.2).
- Use of testosterone with corticosteroids may result in increased fluid retention. Use with caution, particularly in patients with cardiac, renal, or hepatic disease (7.3).

8 USE IN SPECIFIC POPULATIONS

Geriatric Patients: There are insufficient long-term safety data to assess the potential risks of cardiovascular disease and prostate cancer (8.5).

FULL PRESCRIBING INFORMATION

WARNING: SERIOUS PULMONARY OIL MICROEMBOLISM (POME) REACTIONS AND ANAPHYLAXIS

- Serious POME reactions, involving urge to cough, dyspnea, throat tightening, chest pain, dizziness, and syncope; and episodes of anaphylaxis, including life-threatening reactions, have been reported to occur during or immediately after the administration of testosterone undecanoate injection. These reactions can occur after any injection of testosterone undecanoate during the course of therapy, including after the first dose [see Warnings and Precautions (5.1)].
- Following each injection of AVEED, observe patients in the healthcare setting for 30 minutes in order to provide appropriate medical treatment in the event of serious POME reactions or anaphylaxis [see Warnings and Precautions (5.1)].
- Because of the risks of serious POME reactions and anaphylaxis, AVEED is available only through a restricted program under a Risk Evaluation and Mitigation Strategy (REMS) called the AVEED REMS Program [see Warnings and Precautions (5.2)].

1 INDICATIONS AND USAGE

AVEED is indicated for testosterone replacement therapy in adult males for conditions associated with a deficiency or absence of endogenous testosterone.

- Primary hypogonadism (congenital or acquired): testicular failure due to cryptorchidism, bilateral torsion, orchitis, vanishing testis syndrome, orchiectomy, Klinefelter's syndrome, chemotherapy, or toxic damage from alcohol or heavy metals. These men usually have low serum testosterone concentrations and gonadotropins (follicle-stimulating hormone [FSH], luteinizing hormone [LH]) above the normal range.
- Hypogonadotropic hypogonadism (congenital or acquired): gonadotropin or luteinizing hormone-releasing hormone (LHRH) deficiency or pituitary-hypothalamic injury from tumors, trauma, or radiation. These men have low testosterone serum concentrations but have gonadotropins in the normal or low range.

AVEED should only be used in patients who require testosterone replacement therapy and in whom the benefits of the product outweigh the serious risks of POME and anaphylaxis.

Limitations of Use

- Safety and efficacy of AVEED in men with “age-related hypogonadism” (also referred to as “late-onset hypogonadism”) have not been established.
- Safety and efficacy of AVEED in males less than 18 years old have not been established [see Use in Specific Populations (8.4)].

RECENT MAJOR CHANGES

Warnings and Precautions, Venous Thromboembolism (5.4) 07/2025

Warnings and Precautions, Blood Pressure Increases (5.6) 07/2025

Warnings and Precautions, Cardiovascular Risk (5.6) Removed 07/2025

2 DOSAGE AND ADMINISTRATION

Prior to initiating AVEED, confirm the diagnosis of hypogonadism by ensuring that serum testosterone concentrations have been measured in the morning on at least 2 separate days and that these serum testosterone concentrations are below the normal range.

2.1 Dosage

AVEED is for intramuscular use only. Dosage titration is not necessary.

Inject AVEED deeply into the gluteal muscle following the usual precautions for intramuscular administration; care must be taken to avoid intravascular injection [see Dosage and Administration (2.3)]. Intravascular injection of AVEED may lead to POME [see Warnings and Precautions (5.1)].

The recommended dose of AVEED is 3 mL (750 mg) injected intramuscularly, followed by 3 mL (750 mg) injected after 4 weeks, then 3 mL (750 mg) injected every 10 weeks thereafter.

2.2 Preparation Instructions

Parenteral drug products should be inspected visually for particulate matter and discoloration prior to administration, whenever solution and container permit.

Carefully remove the gray plastic cap from the top of the vial by lifting it up from the edges with your fingers or by pushing the bottom edge of the cap upward using the top of your thumb. Remove only the gray plastic cap while leaving the aluminum metal ring and crimp seal around the gray rubber stopper in place. To facilitate the removal of medication from the vial, attach an 18-gauge needle and draw 3 mL of air into the syringe. Hold the needle at a 45° angle to the stopper with the bevel in the up orientation. Inject through the gray rubber stopper into the vial to create positive pressure within the vial chamber.

Withdraw 3 mL (750 mg) of AVEED solution from the vial. Expel excess air bubbles from the syringe. Replace the syringe needle used to draw up the solution from the vial with a new intramuscular needle and inject. Discard any unused portion in the vial.

2.3 Administration Instructions

The site for injection for AVEED is the gluteus medius muscle site located in the upper outer quadrant of the buttock. Care must be taken to avoid the needle hitting the superior gluteal arteries and sciatic nerve. Between consecutive injections, alternate the injection site between left and right buttock.

Figure 1: Identifying the Injection Site

Following antiseptic skin preparation, enter the muscle and maintain the syringe at a 90° angle with the needle in its deeply imbedded position. Grasp the barrel of the syringe firmly with one hand. With the other hand, pull back on the plunger and aspirate for several seconds to ensure that no blood appears. If any blood is drawn into the syringe, immediately withdraw and discard the syringe and prepare another dose.

If no blood is aspirated, reinforce the current needle position to avoid any movement of the needle and slowly (over 60 to 90 seconds) depress the plunger carefully and at a constant rate, until all the medication has been delivered. Be sure to depress the plunger completely with sufficient controlled force. Withdraw the needle.

Immediately upon removal of the needle from the muscle, apply gentle pressure with a sterile pad to the injection site. If there is bleeding at the site of injection, apply a bandage.

Following each injection of AVEED, observe patients in the healthcare setting for 30 minutes in order to provide appropriate medical treatment in the event of serious POME reactions or anaphylaxis [see Warnings and Precautions (5.1)].

3 DOSAGE FORMS AND STRENGTHS

750 mg/3 mL (250 mg/mL) testosterone undecanoate sterile injectable solution is provided in an amber glass, single use vial with silver-colored crimp seal and gray plastic cap.

4 CONTRAINDICATIONS

AVEED should not be used in any of the following patients:

- Men with carcinoma of the breast or known or suspected carcinoma of the prostate [see Warnings and Precautions (5.5)].
- Women who are pregnant. Testosterone can cause virilization of the female fetus when administered to a pregnant woman [see Use in Specific Populations (8.1, 8.2)].
- Men with known hypersensitivity to AVEED or any of its ingredients (testosterone undecanoate, refined castor oil, benzyl benzoate).

5 WARNINGS AND PRECAUTIONS

5.1 Serious Pulmonary Oil Microembolism (POME) Reactions and Anaphylaxis

Serious POME reactions, involving cough, urge to cough, dyspnea, hyperhidrosis, throat tightening, chest pain, dizziness, and syncope, have been reported to occur during or immediately after the injection of intramuscular testosterone undecanoate 1000 mg (4 mL). The majority of these events lasted a few minutes and resolved with supportive measures; however, some lasted up to several hours and some required emergency care and/or hospitalization. To minimize the risk of intravascular injection of AVEED, care should be taken to inject the preparation deeply into the gluteal muscle, being sure to follow the recommended procedure for intramuscular administration [see Dosage and Administration (2.2, 2.3) and Adverse Reactions (6.2)].

In addition to serious POME reactions, episodes of anaphylaxis, including life-threatening reactions, have also been reported to occur following the injection of intramuscular testosterone undecanoate.

Both serious POME reactions and anaphylaxis can occur after any injection of testosterone undecanoate during the course of therapy, including after the first dose. Patients with suspected hypersensitivity reactions to AVEED should not be re-treated with AVEED.

Following each injection of AVEED, observe patients in the healthcare setting for 30 minutes in order to provide appropriate medical treatment in the event of serious POME reactions and anaphylaxis.

5.2 AVEED Risk Evaluation and Mitigation Strategy (REMS) Program

AVEED is available only through a restricted program called the AVEED REMS Program because of the risk of serious POME and anaphylaxis.

Notable requirements of the AVEED REMS Program include the following:

- Healthcare providers who prescribe AVEED must be certified with the REMS Program before ordering or dispensing AVEED.
- Healthcare settings must be certified with the REMS Program and have healthcare providers who are certified before ordering or dispensing AVEED. Healthcare settings must have on-site access to equipment and personnel trained to manage serious POME and anaphylaxis.

Further information is available at www.aveedrems.com or call 1-855-755-0494.

5.3 Polycythemia

Increases in hematocrit, reflective of increases in red blood cell mass, may require discontinuation of testosterone.

Check hematocrit prior to initiating testosterone treatment. It would be appropriate to re-evaluate the hematocrit 3 to 6 months after starting testosterone treatment, and then annually. If hematocrit becomes elevated, stop therapy until hematocrit decreases to an acceptable level. An increase in red blood cell mass may increase the risk of thromboembolic events.

5.4 Venous Thromboembolism (VTE)

There have been postmarketing reports of venous thromboembolic events, including deep vein thrombosis (DVT) and pulmonary embolism (PE), in patients using testosterone products, such as AVEED.

In the Testosterone Replacement therapy for Assessment of long-term Vascular Events and efficacy ResponSE in hypogonadal men (TRAVERSE) Study, a randomized, double-blind, placebo-controlled, cardiovascular (CV) outcomes study, compared to placebo, topical testosterone gel was associated with a numerically higher incidence of VTE (1.7% vs 1.2%) which included DVT (0.6% vs 0.5%) and PE events (0.9% vs 0.5%) [see Adverse Reactions (6.1)].

Evaluate patients who report symptoms of pain, edema, warmth and erythema in the lower extremity for DVT and those who present with acute shortness of breath for PE. If a venous thromboembolic event is suspected, discontinue treatment with AVEED and initiate appropriate workup and management.

5.5 Worsening of Benign Prostatic Hyperplasia (BPH) and Potential Risk of Prostate Cancer

Patients with BPH treated with androgens are at an increased risk of worsening of signs and symptoms of BPH. Monitor patients with BPH for worsening signs and symptoms.

Patients treated with androgens may be at an increased risk for prostate cancer. Evaluate patients for prostate cancer prior to initiating and during treatment with androgens [see Contraindications (4)].

5.6 Blood Pressure Increases

AVEED can increase blood pressure. In an ambulatory blood pressure monitoring (ABPM) study, AVEED increased the mean systolic/diastolic blood pressure by 3.1/2.0 mm Hg from baseline after 16 weeks of treatment. In patients with hypertension on antihypertensive therapy, AVEED increased the mean systolic/diastolic BP by 2.1/1.5 mm Hg from baseline. Blood pressure increases can increase cardiovascular (CV) risk over time.

The CV risk associated with topical testosterone gel was evaluated in TRAVERSE, a randomized, double-blind, placebo-controlled, CV outcomes study in men with a history of CV disease or multiple CV risk factors. In TRAVERSE, topical testosterone gel increased mean systolic blood pressure by 1.0 mm Hg from baseline to 36 months, whereas a mean decrease from baseline of 0.5 mm Hg was observed in the placebo group at this timepoint, for a mean between-group difference of 1.5 mm Hg. However, the incidences of major adverse cardiovascular events (MACE), including cardiovascular death, non-fatal myocardial infarction [MI] and non-fatal stroke, were similar between treatment groups (7% for topical testosterone gel vs 7.3% for placebo) [See Adverse Reactions (6.1)].

Monitor blood pressure periodically in men using AVEED, especially men with hypertension. AVEED is not recommended for use in patients with uncontrolled hypertension.

5.7 Abuse of Testosterone and Monitoring of Serum Testosterone Concentrations

Testosterone has been subject to abuse, typically at doses higher than recommended for the approved indication and in combination with other anabolic androgenic steroids. Anabolic androgenic steroid abuse can lead to serious cardiovascular and psychiatric adverse reactions [see Drug Abuse and Dependence (9)].

If testosterone abuse is suspected, check serum testosterone concentrations to ensure they are within therapeutic range. However, testosterone levels may be in the normal or subnormal range in men abusing synthetic testosterone derivatives. Counsel patients concerning the serious adverse reactions associated with abuse of testosterone and anabolic androgenic steroids. Conversely, consider the possibility of testosterone and anabolic androgenic steroid abuse in suspected patients who present with serious cardiovascular or psychiatric adverse events.

5.8 Not for Use in Women

Due to lack of controlled evaluations in women and potential virilizing effects, AVEED is not indicated for use in women [see Contraindications (4) and Use in Specific Populations (8.1, 8.2)].

5.9 Potential for Adverse Effects on Spermatogenesis

With large doses of exogenous androgens, including AVEED, spermatogenesis may be suppressed through feedback inhibition of pituitary FSH which could possibly lead to adverse effects on semen parameters including sperm count.

5.10 Hepatic Adverse Effects

Prolonged use of high doses of orally active 17-alpha-alkyl androgens (eg, methyltestosterone) has been associated with serious hepatic adverse effects (peliosis hepatis, hepatic neoplasms, cholestatic hepatitis, and jaundice). Peliosis hepatis can be a life threatening or fatal complication. Long-term therapy with intramuscular testosterone enanthate, which elevates blood levels for prolonged periods, has produced multiple hepatic adenomas. AVEED is not known to produce these adverse effects. Nonetheless, patients should be instructed to report any signs or symptoms of hepatic dysfunction (eg, jaundice). If these occur, promptly discontinue AVEED while the cause is evaluated.

5.11 Edema

Androgens, including AVEED, may promote retention of sodium and water. Edema with or without congestive heart failure may be a serious complication in patients with preexisting cardiac, renal, or hepatic disease. In addition to discontinuation of the drug, diuretic therapy may be required.

5.12 Gynecomastia

Gynecomastia occasionally develops and occasionally persists in patients being treated for hypogonadism [see Adverse Reactions (6.1)].

5.13 Sleep Apnea

The treatment of hypogonadal men with testosterone products may potentiate sleep apnea in some patients, especially those with risk factors such as obesity or chronic lung diseases.

5.14 Lipid Changes

Changes in serum lipid profile may require dose adjustment of lipid lowering drugs or discontinuation of testosterone therapy, such as AVEED. Monitor the lipid profile periodically, particularly after starting testosterone therapy.

5.15 Hypercalcemia

Androgens, including AVEED, should be used with caution in cancer patients at risk of hypercalcemia (and associated hypercalciuria). Regular monitoring of serum calcium concentrations is recommended in these patients.

5.16 Decreased Thyroxine-binding Globulin

Androgens, including AVEED, may decrease concentrations of thyroxine-binding globulin, resulting in decreased total T4 serum concentrations and increased resin uptake of T3 and T4. Free thyroid hormone concentrations remain unchanged, however, and there is no clinical evidence of thyroid dysfunction.

6 ADVERSE REACTIONS

6.1 Clinical Trial Experience

Because clinical trials are conducted under widely varying conditions, adverse reaction rates observed in the clinical trials of a drug cannot be directly compared to rates in the clinical trials of another drug and may not reflect the rates observed in clinical practice.

AVEED was evaluated in an 84-week clinical study using a dose regimen of 750 mg (3 mL) at initiation, at 4 weeks, and every 10 weeks thereafter in 153 hypogonadal men. The most commonly reported adverse reactions (>2%) were: acne (5.2%), injection site pain (4.6%), prostate specific antigen increased (4.6%), hypogonadism (2.6%) and estradiol increased (2.6%).

Table 1 presents adverse reactions reported by ≥1% of patients in the 84-week clinical study.

Table 1: Adverse Reactions Reported in at Least 1% of Patients in the 84-Week Clinical Study of AVEED

MedDRA Preferred Term | Number of Patients (%)
MedDRA Preferred Term | AVEED 750 mg (N=153)
Acne | 8 (5.2%)
Injection site pain | 7 (4.6%)
Prostatic specific antigen increased* | 7 (4.6%)
Estradiol increased | 4 (2.6%)
Hypogonadism | 4 (2.6%)
Fatigue | 3 (2%)
Irritability | 3 (2%)
Hemoglobin increased | 3 (2%)
Insomnia | 3 (2%)
Mood swings | 3 (2%)
Aggression | 2 (1.3%)
Ejaculation disorder | 2 (1.3%)
Injection site erythema | 2 (1.3%)
Hematocrit increased | 2 (1.3%)
Hyperhidrosis | 2 (1.3%)
Prostate Cancer | 2 (1.3%)
Prostate induration | 2 (1.3%)
Weight increased | 2 (1.3%)

*Prostate-specific antigen increased defined as a serum PSA concentration >4 ng/mL.

In the 84-week clinical trial, 7 patients (4.6%) discontinued treatment because of adverse reactions. Adverse reactions leading to discontinuation included: hematocrit increased, estradiol increased, prostatic specific antigen increased, prostate cancer, mood swings, prostatic dysplasia, acne, and deep vein thrombosis.

During the 84-week clinical trial, the average serum PSA increased from 1.0 ± 0.8 ng/mL at baseline to 1.5 ± 1.3 ng/mL at the end of study. Fourteen (14) patients (10.9%) in whom the baseline PSA was < 4 ng/mL had a post-baseline serum PSA of > 4 ng/mL during the 84-week treatment period.

A total of 725 hypogonadal men received intramuscular testosterone undecanoate in a total of 7 controlled clinical trials. In these clinical trials, the dose and dose frequency of intramuscular testosterone undecanoate varied from 750 mg to 1000 mg, and from every 9 weeks to every 14 weeks. Several of these clinical trials incorporated additional doses upon initiation of therapy (eg, loading doses). In addition to those adverse reactions noted in Table 1, the following adverse events were reported by at least 3% of patients in these trials, irrespective of the investigator’s assessment of relationship to study medication: sinusitis, prostatitis, arthralgia, nasopharyngitis, upper respiratory tract infection, bronchitis, back pain, hypertension, diarrhea and headache.

Pulmonary Oil Microembolism (POME) and Anaphylaxis in Controlled Clinical Studies

Adverse events attributable to POME and anaphylaxis were reported in a small number of patients in controlled clinical trials. In the 84-week clinical trial of AVEED, 1 patient experienced a mild coughing fit lasting 10 minutes after his third injection, which was retrospectively attributed to POME. In another clinical trial of intramuscular testosterone undecanoate (1000 mg), a hypogonadal male patient experienced the urge to cough and respiratory distress at 1 minute after his tenth injection, which was also retrospectively attributed to POME.

During a review that involved adjudication of all cases meeting specific criteria, 9 POME events in 8 patients and 2 events of anaphylaxis among 3,556 patients treated with intramuscular testosterone undecanoate in 18 clinical trials were judged to have occurred.

Blood Pressure Increases

In a 4-month clinical study, 24-hour ambulatory blood pressure monitoring (ABPM) was conducted on 222 patients. ABPM was conducted at baseline and at Week 16 of AVEED therapy. A total of 139 patients had acceptable ABPM recordings at both baseline and Week 16 and were at least 85% compliant with study drug. In that group, the mean change in 24-hour systolic blood pressure (BP) and diastolic BP from baseline to end-of-treatment at Week 16 (n=139) was 3.1 mm Hg (95% CI 1.2, 4.9) and 2.0 mm Hg (95% CI 0.9, 3.1), respectively. In patients with a history of hypertension who were receiving antihypertensive therapy, the mean ABPM systolic and diastolic BP increased by 2.1 mm Hg [95% CI -0.7, 5.0] and 1.5 mm Hg [95% CI -0.1, 3.2], respectively [n=73]). In patients with no history of hypertension, the mean systolic and diastolic blood pressure increased by 3.3 mm Hg [95% CI 0.8, 5.8] and 2.5 mm Hg [95% CI 1.0, 4.0], respectively [n=65].

2 patients (1.4%) on AVEED, both of whom were receiving antihypertensive medications at baseline, either started new antihypertensive medications (n=2) or had their antihypertensive medication regimen adjusted (n=0) during the ABPM study.

Of the 222 patients in the ABPM study who used AVEED, 8 patients (3.6%) were reported to have either an adverse reaction of hypertension (7 patients, 3.2%) or increased blood pressure (1 patient, 0.4%).

Cardiovascular Outcomes

TRAVERSE was a randomized, double-blind, cardiovascular outcomes study to assess the cardiovascular (CV) safety of topical testosterone gel compared to placebo in 5198 hypogonadal men aged 45 to 80 years with a history of CV disease or with multiple CV risk factors. The primary outcome was the incidence of the composite endpoint of major adverse cardiovascular events (MACE), consisting of CV death, non-fatal myocardial infarction (MI), and non-fatal stroke.

The mean duration of therapy was approximately 22 months. The mean duration of follow-up was 33 months. Approximately 61% of all patients discontinued topical testosterone gel or placebo therapy.

The mean patient age (±SD) was 63.3 (7.9) years, with 2452 patients aged 65 years or more (47%); 2847 (about 55%) patients had pre-existing cardiovascular disease, whereas 2357 patients (about 45%) had an elevated cardiovascular risk at baseline, and mean BMI was 35 kg/m^2. Approximately 80% of patients were White, 17% were Black, and 3% were of other races or ethnic groups. Approximately 69%, 84%, and 93% had diabetes mellitus, hyperlipidemia, and hypertension, respectively.

The mean serum testosterone concentration at baseline in patients receiving topical testosterone gel was 220.4 ng/dL (n=2596). The mean serum testosterone concentrations at 12 months, 24 months, 36 months, and 48 months in patients receiving topical testosterone gel were 440.5 ng/dL (n=1683), 420.9 ng/dl (n=1125), 428.7 ng/dL (n=731), and 365.2 ng/dL (n=220), respectively.

For patients treated with topical testosterone gel, the incidence of MACE was 7.0% (n=182 events) and for those receiving placebo, the incidence of MACE was 7.3% (n=190 events). The study demonstrated non-inferiority of topical testosterone gel versus placebo because the upper bound of 95% CI was less than the pre-specified risk margin, of 1.5 for MACE (Hazard Ratio 0.96 [95% CI: 0.78, 1.17]).

Additional Adverse Reactions Reported in TRAVERSE

Additional adverse reactions reported in TRAVERSE at an incidence rate >2% in either treatment group and greater in topical testosterone gel versus placebo included: nonfatal arrythmias warranting intervention (5.2% vs 3.3%), atrial fibrillation (3.5% vs 2.4%), acute kidney injury (2.3% vs 1.5%) and bone fracture (3.5% vs 2.5%). For the adverse reaction of bone fracture, each event was adjudicated by clinical review.

6.2 Postmarketing Experience

The following adverse reactions have been identified during post-approval use of AVEED. Because the reactions are reported voluntarily from a population of uncertain size, it is not always possible to reliably estimate their frequency or establish a causal relationship to drug exposure.

Pulmonary Oil Microembolism (POME) and Anaphylaxis

Serious POME reactions, involving cough, urge to cough, dyspnea, hyperhidrosis, throat tightening, chest pain, dizziness, and syncope, have been reported to occur during or immediately after the injection of intramuscular testosterone undecanoate 1000 mg (4 mL) in post-approval use outside the United States. The majority of these events lasted a few minutes and resolved with supportive measures; however, some lasted up to several hours and some required emergency care and/or hospitalization.

In addition to serious POME reactions, episodes of anaphylaxis, including life-threatening reactions, have also been reported to occur following the injection of intramuscular testosterone undecanoate in post-approval use outside of the United States.

Both serious POME reactions and anaphylaxis have been reported to occur after any injection of testosterone undecanoate during the course of therapy, including after the first dose.

Other Events

The following treatment emergent adverse events or adverse reactions have been identified during post-marketing clinical trials and during post-approval use of intramuscular testosterone undecanoate. In most cases, the dose being used was 1000 mg.

Blood and Lymphatic System Disorders: polycythemia, thrombocytopenia

Cardiac Disorders: angina pectoris, cardiac arrest, cardiac failure, coronary artery disease, coronary artery occlusion, myocardial infarction, tachycardia

Ear and Labyrinth Disorders: sudden hearing loss, tinnitus

Endocrine Disorders: hyperparathyroidism, hypoglycemia

Gastrointestinal Disorders: abdominal pain upper, diarrhea, vomiting

General Disorders and Administrative Site Conditions: chest pain, edema peripheral, injection site discomfort, injection site hematoma, injection site irritation, injection site pain, injection site reaction, malaise, paresthesia, procedural pain

Immune System Disorders: anaphylactic reaction, anaphylactic shock, asthma, dermatitis allergic, hypersensitivity, leukocytoclastic vasculitis

Infections and Infestations: injection site abscess, prostate infection

Investigations: alanine aminotransferase increased, aspartate aminotransferase increased, blood bilirubin increased, blood glucose increased, blood pressure increased, blood prolactin increased, blood testosterone decreased, blood testosterone increased, blood triglycerides increased, gamma-glutamyltransferase increased, hematocrit increased, intraocular pressure increased, liver function test abnormal, prostate examination abnormal, prostatic specific antigen increased, transaminases increased

Metabolism and Nutrition Disorders: diabetes mellitus, fluid retention, hyperlipidemia, hypertriglyceridemia

Musculoskeletal and Connective Tissue Disorders: musculoskeletal chest pain, musculoskeletal pain, myalgia, osteopenia, osteoporosis, systemic lupus erythematosus

Neoplasms Benign, Malignant and Unspecified (including cysts and polyps): prostate cancer, prostatic intraepithelial neoplasia

Nervous System Disorders: stroke, cerebrovascular insufficiency, reversible ischemic neurological deficiency, transient ischemic attack

Psychiatric Disorders: aggression, anxiety, depression, insomnia, irritability, Korsakoff’s psychosis non-alcoholic, male orgasmic disorder, nervousness, restlessness, sleep disorder

Renal and Urinary Disorders: calculus urinary, dysuria, hematuria, nephrolithiasis, pollakiuria, renal colic, renal pain, urinary tract disorder

Reproductive System and Breast Disorders: azoospermia, benign prostatic hyperplasia, breast induration, breast pain, erectile dysfunction, gynecomastia, libido decreased, libido increased, prostate induration, prostatitis, spermatocele, testicular pain

Respiratory, Thoracic and Mediastinal Disorders: asthma, chronic obstructive pulmonary disease, cough, dysphonia, dyspnea, hyperventilation, obstructive airway disorder, pharyngeal edema, pharyngolaryngeal pain, pulmonary microemboli, pulmonary embolism, respiratory distress, rhinitis, sleep apnea syndrome, snoring

Skin and Subcutaneous Tissue Disorders: acne, alopecia, angioedema, angioneurotic edema, dermatitis allergic, erythema, hyperhidrosis, pruritus, rash

Vascular Disorders: cerebral infarction, cerebrovascular accident, circulatory collapse, deep venous thrombosis, hot flush, hypertension, syncope, thromboembolism, thrombosis, venous insufficiency

7 DRUG INTERACTIONS

7.1 Insulin

Changes in insulin sensitivity or glycemic control may occur in patients treated with androgens. In diabetic patients, the metabolic effects of androgens may decrease blood glucose and, therefore, may necessitate a decrease in the dose of anti-diabetic medication.

7.2 Oral Anticoagulants

Changes in anticoagulant activity may be seen with androgens, therefore more frequent monitoring of international normalized ratio (INR) and prothrombin time are recommended in patients taking warfarin, especially at the initiation and termination of androgen therapy.

7.3 Corticosteroids

The concurrent use of testosterone with corticosteroids may result in increased fluid retention and requires careful monitoring, particularly in patients with cardiac, renal or hepatic disease.

8 USE IN SPECIFIC POPULATIONS

8.1 Pregnancy

Risk Summary

AVEED is contraindicated in pregnant women. Testosterone is teratogenic and may cause fetal harm based on data from animal studies and its mechanism of action [see Contraindications (4) and Clinical Pharmacology (12.1)]. Exposure of a female fetus to androgens may result in varying degrees of virilization. In animal development studies, exposure to testosterone in utero resulted in hormonal and behavioral changes in offspring and structural impairments of reproductive tissues in female and male offspring. These studies did not meet current standards for nonclinical development toxicity studies.

Data

Animal Data

In developmental studies conducted in rats, rabbits, pigs, sheep and rhesus monkeys, pregnant animals received intramuscular injection of testosterone during the period of organogenesis. Testosterone treatment at doses that were comparable to those used for testosterone replacement therapy resulted in structural impairments in both female and male offspring. Structural impairments observed in females included increased anogenital distance, phallus development, empty scrotum, no external vagina, intrauterine growth retardation, reduced ovarian reserve, and increased ovarian follicular recruitment. Structural impairments seen in male offspring included increased testicular weight, larger seminal tubular lumen diameter, and higher frequency of occluded tubule lumen. Increased pituitary weight was seen in both sexes.

Testosterone exposure in utero also resulted in hormonal and behavioral changes in offspring. Hypertension was observed in pregnant female rats and their offspring exposed to doses approximately twice those used for testosterone replacement therapy.

8.2 Lactation

Risk Summary

AVEED is not indicated for use in females.

8.3 Females and Males of Reproductive Potential

Infertility

During treatment with large doses of exogenous androgens, including AVEED, spermatogenesis may be suppressed through feedback inhibition of the hypothalamic-pituitary-testicular axis [see Warnings and Precautions (5.9)], possibly leading to adverse effects on semen parameters including sperm count. Reduced fertility is observed in some men taking testosterone replacement therapy. Testicular atrophy, subfertility, and infertility have also been reported in men who abuse anabolic androgenic steroids [see Drug Abuse and Dependence (9.2)]. With either type of use, the impact on fertility may be irreversible.

8.4 Pediatric Use

Safety and effectiveness of AVEED in pediatric patients less than 18 years old have not been established. Improper use may result in acceleration of bone age and premature closure of epiphyses.

8.5 Geriatric Use

There have not been sufficient numbers of geriatric patients in controlled clinical studies with AVEED to determine whether efficacy or safety in those over 65 years of age differs from younger subjects. Of the 153 patients enrolled in the pivotal clinical study utilizing AVEED, 26 (17.0%) were over 65 years of age. Additionally, there are insufficient long-term safety data in geriatric patients to assess the potentially increased risk of cardiovascular disease and prostate cancer.

Geriatric patients treated with androgens may also be at risk for worsening of signs and symptoms of BPH [see Warnings and Precautions (5.5)].

8.6 Renal Impairment

No studies were conducted in patients with renal impairment.

8.7 Hepatic Impairment

No studies were conducted in patients with hepatic impairment.

9 DRUG ABUSE AND DEPENDENCE

9.1 Controlled Substance

AVEED contains testosterone, a Schedule III controlled substance in the Controlled Substances Act.

9.2 Abuse

Drug abuse is intentional non-therapeutic use of a drug, even once, for its rewarding psychological and physiological effects. Abuse and misuse of testosterone are seen in male and female adults and adolescents. Testosterone, often in combination with other anabolic androgenic steroids (AAS), and not obtained by prescription through a pharmacy, may be abused by athletes and bodybuilders. There have been reports of misuse of men taking higher doses of legally obtained testosterone than prescribed and continuing testosterone despite adverse events or against medical advice.

Abuse-Related Adverse Reactions

Serious adverse reactions have been reported in individuals who abuse anabolic androgenic steroids, and include cardiac arrest, myocardial infarction, hypertrophic cardiomyopathy, congestive heart failure, cerebrovascular accident, hepatotoxicity, and serious psychiatric manifestations, including major depression, mania, paranoia, psychosis, delusions, hallucinations, hostility, and aggression.

The following adverse reactions have also been reported in men: transient ischemic attacks, convulsions, hypomania, irritability, dyslipidemias, testicular atrophy, subfertility, and infertility.

The following additional adverse reactions have been reported in women: hirsutism, virilization, deepening of voice, clitoral enlargement, breast atrophy, male-pattern baldness, and menstrual irregularities.

The following adverse reactions have been reported in male and female adolescents: premature closure of bony epiphyses with termination of growth, and precocious puberty.

Because these reactions are reported voluntarily from a population of uncertain size and may include abuse of other agents, it is not always possible to reliably estimate their frequency or establish a causal relationship to drug exposure.

9.3 Dependence

Behaviors Associated with Addiction

Continued abuse of testosterone and other anabolic steroids, leading to addiction is characterized by the following behaviors:

- Taking greater dosages than prescribed
- Continued drug use despite medical and social problems due to drug use
- Spending significant time to obtain the drug when supplies of the drug are interrupted
- Giving a higher priority to drug use than other obligations
- Having difficulty in discontinuing the drug despite desires and attempts to do so
- Experiencing withdrawal symptoms upon abrupt discontinuation of use

Physical dependence is characterized by withdrawal symptoms after abrupt drug discontinuation or a significant dose reduction of a drug. Individuals taking supratherapeutic doses of testosterone may experience withdrawal symptoms lasting for weeks or months which include depressed mood, major depression, fatigue, craving, restlessness, irritability, anorexia, insomnia, decreased libido, and hypogonadotropic hypogonadism.

Drug dependence in individuals using approved doses of testosterone for approved indications has not been documented.

10 OVERDOSAGE

There have been no reports of overdosage in the AVEED clinical trials. There is 1 report of acute overdosage with use of an approved injectable testosterone product: this subject had serum testosterone levels of up to 11,400 ng/dL with a cerebrovascular accident.

Treatment of overdosage would consist of discontinuation of AVEED together with appropriate symptomatic and supportive care.

11 DESCRIPTION

AVEED (testosterone undecanoate) injection contains testosterone undecanoate (17β-undecanoyloxy-4-androsten-3-one) which is an ester of the androgen, testosterone. Testosterone is formed by cleavage of the ester side chain of testosterone undecanoate.

Testosterone undecanoate is a white to off-white crystalline substance. The empirical formula of testosterone undecanoate is C30H48O3 and a molecular weight of 456.7. The structural formula is:

Figure 2: Testosterone Undecanoate

C30H48O3 MW: 456.7

AVEED is a clear, yellowish, sterile oily solution containing testosterone undecanoate, a testosterone ester, for intramuscular injection. Each single use vial contains 3 mL of 250 mg/mL testosterone undecanoate solution in a mixture of 1500 mg of benzyl benzoate and 885 mg of refined castor oil.

12 CLINICAL PHARMACOLOGY

12.1 Mechanism of Action

Endogenous androgens, including testosterone and dihydrotestosterone (DHT) are responsible for the normal growth and development of the male sex organs and for maintenance of secondary sex characteristics. These effects include the growth and maturation of prostate, seminal vesicles, penis, and scrotum; the development of male hair distribution, such as facial, pubic, chest, and axillary hair; laryngeal enlargement; vocal cord thickening; and alterations in body musculature and fat distribution.

Male hypogonadism, a clinical syndrome resulting from insufficient secretion of testosterone, has 2 main etiologies. Primary hypogonadism is caused by defects of the gonads, such as Klinefelter’s syndrome or Leydig cell aplasia, whereas secondary hypogonadism is the failure of the hypothalamus (or pituitary) to produce sufficient gonadotropins (FSH, LH).

12.3 Pharmacokinetics

Absorption

AVEED 750 mg delivers physiologic amounts of testosterone, producing circulation testosterone concentrations that approximate normal concentrations (300-1000 ng/dL) seen in healthy men.

Testosterone esters in oil injected intramuscularly are absorbed from the lipid phase. Cleavage of the undecanoic acid side chain of AVEED by tissue esterases releases testosterone.

Following intramuscular injection of 750 mg of AVEED, serum testosterone concentrations reach a maximum after a median of 7 days (range 4 to 42 days) then slowly decline (Figure 3). Steady-state serum testosterone concentration was achieved with the third injection of AVEED at 14 weeks.

Figure 3 shows the mean serum total testosterone concentration-time profile during the third injection interval (at steady state, 14 to 24 weeks) for hypogonadal men (less than 300 ng/dL) given 750 mg AVEED at initiation, at 4 weeks, and every 10 weeks thereafter. Intramuscular injection of 750 mg of AVEED generates mean steady-state serum total testosterone concentrations in the normal range for 10 weeks.

Figure 3: Mean (SD) Serum Total Testosterone
Concentrations (ng/dL) at 14 to 24 Weeks

Distribution

Circulating testosterone is chiefly bound in the serum to sex hormone-binding globulin (SHBG) and albumin.

Approximately 40% of testosterone in plasma is bound to SHBG, 2% remains unbound (free), and the rest is loosely bound to albumin and other proteins.

Metabolism

Testosterone undecanoate is metabolized to testosterone via ester cleavage of the undecanoate group. The mean (SD) maximum concentration of testosterone undecanoate was 90.9 (68.8) ng/dL on Day 4 following injection of AVEED. Testosterone undecanoate was nearly undetectable 42 days following injection of AVEED.

Testosterone is metabolized to various 17-keto steroids through 2 different pathways. The major active metabolites of testosterone are estradiol and DHT.

DHT concentrations increased in parallel with testosterone concentrations during AVEED treatment. Average DHT concentrations during a dosing interval ranged from 244 to 451 ng/dL. The mean DHT to testosterone ratios ranged from 0.05 to 0.07.

Excretion

There is considerable variation in the half-life of testosterone as reported in the literature, ranging from 10 to 100 minutes. About 90% of a testosterone dose given intramuscularly is excreted in the urine as glucuronic and sulfuric acid-conjugates of testosterone or as metabolites. About 6% of a dose is excreted in the feces, mostly in the unconjugated form. Inactivation of testosterone occurs primarily in the liver.

Effect of Body Weight and Body Mass Index (BMI)

Analysis of serum testosterone concentrations from 117 hypogonadal men in the 84-week clinical study of AVEED indicated that serum testosterone concentrations achieved were inversely correlated with the patient’s body weight. In 60 patients with pretreatment body weight of ≥100 kg, the mean (±SD) serum testosterone average concentration was 426 ± 104 ng/dL. A higher serum testosterone average concentration (568 ± 139 ng/dL) was observed in 57 patients weighing 65 to 100 kg. A similar trend was also observed for maximum serum testosterone concentrations.

In 70 patients with pretreatment BMIs of >30 kg/m^2, the mean (±SD) serum testosterone average concentration was 445 ± 116 ng/dL. Higher serum testosterone average concentrations (579 ± 101 ng/dL and 567± 155ng/dL) were observed in patients with BMIs <26 kg/m^2 and 26 to 30 kg/m^2, respectively. A similar trend was also observed for maximum serum testosterone concentrations.

13 NONCLINICAL TOXICOLOGY

13.1 Carcinogenesis, Mutagenesis, Impairment of Fertility

Carcinogenesis

Testosterone has been tested by subcutaneous injection and implantation in mice and rats. In mice, the implant induced cervical-uterine tumors, which metastasized in some cases. There is suggestive evidence that injection of testosterone into some strains of female mice increases their susceptibility to hepatoma. Testosterone is also known to increase the number of tumors and decrease the degree of differentiation of chemically induced carcinomas of the liver in rats.

Mutagenesis

AVEED was negative in the in vitro Ames assays, the chromosomal aberration assay in human lymphocytes, and in the in vivo mouse micronucleus assay.

Impairment of Fertility

The administration of exogenous testosterone has been reported to suppress spermatogenesis in the rat, dog, and non-human primates, which was reversible on cessation of the treatment.

14 CLINICAL STUDIES

14.1 Testosterone Replacement Therapy

AVEED was evaluated for efficacy in an 84-week, single-arm, open-label, multicenter study of 130 hypogonadal men. Eligible patients weighed at least 65 kg, were 18 years of age and older (mean age 54.2 years), and had a morning serum total testosterone concentration <300 ng/dL (mean screening testosterone concentration 215 ng/dL). Patients were caucasian (74.6%), black (12.3%), Hispanic (10.8%), and of other ethnicities (2.3%). The mean BMI was 32 kg/m^2.

All patients received injections of AVEED 750 mg at baseline, at 4 weeks, and then every 10 weeks thereafter.

The primary endpoint was the percentage of patients with average serum total testosterone concentration (Cavg) within the normal range (300-1000 ng/dL) after the third injection, at steady state.

The secondary endpoint was the percentage of patients with maximum total testosterone concentration (Cmax) above 3 pre-determined limits: greater than 1500 ng/dL, between 1800 and 2499 ng/dL, and greater than 2500 ng/dL.

A total of 117 out of 130 hypogonadal men completed study procedures through Week 24 and were included in the evaluation of testosterone pharmacokinetics after the third AVEED injection. Ninety-four percent (94%) of patients maintained a Cavg within the normal range (300 to 1000 ng/dL). The percentages of patients with Cavg below the normal range (less than 300 ng/dL) and above the normal range (greater than 1000 ng/dL) were 5.1% and 0.9%, respectively.

Table 2 summarizes the mean (SD) serum total testosterone pharmacokinetic parameters at steady state for these 117 patients.

Table 2: Mean (SD) Serum Total Testosterone Concentrations at Steady State

 | AVEED 750 mg; (N=117)
Cavg (0 to 10 weeks) (ng/dL) | 495 (142)
Cmax (ng/dL) | 891 (345)
Cmin (ng/dL) | 324 (99)

Cavg = average concentration; Cmax = maximum concentration; Cmin = minimum concentration

The percentage of patients with Cmax >1500 ng/dL was 7.7%. No patient had a Cmax > 1800 ng/dL.

16 HOW SUPPLIED/STORAGE AND HANDLING

AVEED, NDC 67979-511-43: 750 mg/3 mL (250 mg/mL) testosterone undecanoate sterile injectable solution is provided in an amber glass vial with silver-colored crimp seal and gray plastic cap. Each vial is individually packaged in a carton box.

Store at controlled room temperature 25ºC (77ºF); excursions permitted to 15ºC to 30ºC (59ºF to 86ºF) [See USP controlled room temperature] in its original carton until the date indicated.

Before use, each vial should be visually inspected. Only vials free from particles should be used.

Single Use Vial. Discard unused portion.

17 PATIENT COUNSELING INFORMATION

Advise the patient to read the FDA-approved patient labeling (Medication Guide).

Advise patients of the following:

17.1 Risks of Serious Pulmonary Oil Microembolism (POME) and Anaphylaxis

- Serious POME reactions, involving cough, urge to cough, shortness of breath, sweating, throat tightening, chest pain, dizziness, and syncope, have been reported to occur during or immediately after the injection of intramuscular testosterone undecanoate. The majority of these events lasted a few minutes and resolved with supportive measures; however, some lasted up to several hours and some required emergency care and/or hospitalization.
- Episodes of anaphylaxis, including life-threatening reactions, have also been reported to occur following the injection of intramuscular testosterone undecanoate.
- Both serious POME reactions and anaphylaxis can occur after any injection of testosterone undecanoate during the course of therapy, including after the first dose.
- Advise the patient to read the AVEED REMS information sheet titled "What You Need to Know About AVEED® Treatment: A Patient Guide".
- Instruct patients to remain at the healthcare setting for 30 minutes after each AVEED injection.

17.2 Men with Known or Suspected Carcinoma of the Prostate or Breast

Men with known or suspected prostate or breast cancer should not use AVEED [see Contraindications (4)].

17.3 Potential Adverse Reactions to Androgens

Patients should be informed that treatment with androgens may lead to adverse reactions which include:

- Changes in urinary habits, such as increased urination at night, trouble starting the urine stream, passing urine many times during the day, having an urge to go the bathroom right away, having a urine accident, or being unable to pass urine or weak urine flow
- Breathing disturbances, including those associated with sleep or excessive daytime sleepiness
- Too frequent or persistent erections of the penis
- Nausea, vomiting, changes in skin color, or ankle swelling
- Venous thromboembolism, the signs and symptoms of which may include lower limb pain, edema, or erythema; dyspnea; or chest pain.
- Increased blood pressure that can increase cardiovascular risk over time

17.4 Patients Should Be Advised of the Following Instructions for Use

- Read the Medication Guide before starting AVEED therapy and reread the Guide before each injection.
- Adhere to all recommended monitoring.
- Report any changes in their state of health, such as signs and symptoms of venous thromboembolism, changes in urinary habits, breathing, sleep, and mood.
- Be aware of the importance of monitoring BP periodically while on AVEED. If BP increases while on AVEED, antihypertensive medications may need to be started, added, or adjusted, or AVEED may need to be discontinued.

Manufactured for:
Endo USA
Malvern, PA 19355

© 2025 Endo, Inc. or one of its affiliates.

Revised: 07/2025

MEDICATION GUIDE

AVEED® (Uh-Veed)
(testosterone undecanoate)
injection

Read this Medication Guide before you receive AVEED and before each injection. There may be new information. This Medication Guide does not take the place of talking with your doctor about your medical condition or your treatment.

What is the most important information I should know about AVEED?
AVEED may cause serious side effects, including:

- A serious lung problem. AVEED can cause a serious lung problem called a pulmonary oil microembolism (POME) reaction. POME is caused by tiny droplets of oil that have traveled to the lungs. Symptoms of a POME reaction may include:

o cough or urge to cough

o difficulty breathing

o sweating

o tightening of your throat

o chest pain

o dizziness

o fainting

- Serious allergic reactions (anaphylaxis). AVEED can cause a serious allergic reaction right after receiving the injection. Some of these allergic reactions may be life threatening.

These reactions can happen after you receive your first dose of AVEED or may happen after receiving more than 1 dose.

You may need emergency treatment in a hospital, especially if these symptoms get worse over the 24 hours after your AVEED injection.

These side effects may happen during or right after each injection. To be sure that you are not having one of these reactions:

o You need to stay in the doctor’s office, clinic, or hospital for 30 minutes after having your AVEED injection so that your doctor can watch you for symptoms of POME or a serious allergic reaction.

o You can only get AVEED at your doctor’s office, clinic, or hospital.

AVEED is only available through a restricted program called the AVEED Risk Evaluation and Mitigation Strategy (REMS) Program. For more information about the AVEED REMS Program go to www.AveedREMS.com or call 1-855-755-0494.

What is AVEED?
AVEED is a prescription medicine that contains testosterone. AVEED is used to treat adult males who have low or no testosterone due to certain medical conditions.

AVEED is only for adult males who need testosterone replacement therapy and when the benefit of receiving AVEED is more than the risk of POME and anaphylaxis.

Your healthcare provider will test your blood before you start and while you are taking AVEED.

It is not known if AVEED is safe or effective to treat men who have low testosterone due to aging.

It is not known if AVEED is safe and effective for use in children younger than 18 years old. Improper use of AVEED may affect bone growth in children.

AVEED is a controlled substance (CIII) because it contains testosterone that can be a target for people who abuse prescription medicines.

AVEED is not meant for use in women.

Who should not receive AVEED?
Do not receive AVEED if you:

- have breast cancer
- have or might have prostate cancer
- are pregnant. AVEED may harm your unborn baby.
- are allergic to AVEED or to any of the ingredients in AVEED. See the end of this leaflet for a complete list of ingredients in AVEED.

Talk to your doctor before receiving this medicine if you have any of the above conditions.

What should I tell my doctor before receiving AVEED?
Before receiving AVEED, tell your doctor if you:

- have breast cancer
- have or might have prostate cancer
- have urinary problems due to an enlarged prostate
- have high blood pressure or are being treated for high blood pressure
- have heart problems
- have liver or kidney problems
- have problems breathing while you sleep (sleep apnea)
- have any other medical conditions

Tell your doctor about all the medicines you take, including prescription and over-the-counter medicines, vitamins, and herbal supplements.

Receiving AVEED with certain other medicines can affect each other. Especially tell your doctor if you take:

- insulin
- medicines that decrease blood clotting
- corticosteroids

Ask your doctor or pharmacist for a list of these medicines, if you are not sure.

Know the medicines you take. Keep a list of your medicines and show them to your doctor and pharmacist when you get a new medicine.

How will I receive AVEED?
See “What is the most important information I should know about AVEED?”

Your doctor will inject AVEED deep into the muscle of your buttock. You will get 1 injection when you start, 1 injection 4 weeks later, and then 1 injection every 10 weeks.

Your doctor will test your blood before you receive and while you are receiving AVEED.

What are the possible side effects of AVEED?
AVEED can cause serious side effects including:

- see “What is the most important information I should know about AVEED?”
- if you already have enlargement of your prostate gland, your signs and symptoms can get worse while receiving AVEED. This can include:

o increased urination at night
o trouble starting your urine stream
o having to pass urine many times during the day
o having an urge that you have to go to the bathroom right away
o having a urine accident
o being unable to pass urine or weak urine flow

- changes in certain blood tests
- possible increased risk of prostate cancer. Your doctor should check you for prostate cancer or any other prostate problems before you receive and while you are receiving AVEED.
- blood clots in the legs or lungs. Signs and symptoms of a blood clot in your leg can include leg pain, swelling or redness. Signs and symptoms of a blood clot in your lungs can include difficulty breathing or chest pain.
- Increased blood pressure. AVEED can increase your blood pressure, which can increase your risk of having a heart attack or stroke over time. Your risk may be greater if you have already had a heart attack or stroke or if you have other risk factors for heart attack or stroke. You may need to start new medicines or have medicines changed for high blood pressure while on AVEED. If your blood pressure cannot be controlled, AVEED may need to be stopped. Your healthcare provider should check your blood pressure while you use AVEED.
- in large doses AVEED may lower your sperm count.
- liver problems. Symptoms of liver problems may include:

o nausea or vomiting
o yellowing of your skin or whites of your eyes
o dark urine
o pain on the right side of your stomach area (abdominal pain)

- swelling of your ankles, feet, or body, with or without heart failure. This may cause serious problems for people who have heart, kidney, or liver disease.
- enlarged or painful breasts.
- have problems breathing while you sleep (sleep apnea).

Call your doctor right away if you have any of the serious side effects listed above.

The most common side effects of AVEED include:

- acne
- pain at the injection site
- increased prostate specific antigen (a test used to screen for prostate cancer)
- increased estradiol level
- low testosterone level
- feeling tired
- irritability
- increased red blood cell count
- difficulty sleeping
- mood swings

Other side effects include more erections than are normal for you or erections that last for a long time.

Tell your doctor if you have any side effect that bothers you or that does not go away.

These are not all the possible side effects with AVEED. For more information, ask your doctor or pharmacist.

Call your doctor for medical advice about side effects. You may report side effects to FDA at 1-800-FDA-1088.

General information about AVEED

Medicines are sometimes prescribed for purposes other than those listed in a Medication Guide.

This Medication Guide summarizes the most important information about AVEED. If you would like more information, talk with your doctor. You can ask your doctor or nurse for information about AVEED that is written for health professionals. For more information, go to www.AVEEDUSA.com or call 1-800-462-3636.

What are the ingredients in AVEED?
Active ingredient: testosterone undecanoate
Inactive ingredients: benzyl benzoate, refined castor oil

This Medication Guide has been approved by the U.S. Food and Drug Administration.

Manufactured for:
Endo USA
Malvern, PA 19355

© 2025 Endo, Inc. or one of its affiliates.

Revised: 07/2025

Principle Display Panel - Vial Label

PACKAGE LABEL

Principle Display Panel - Carton